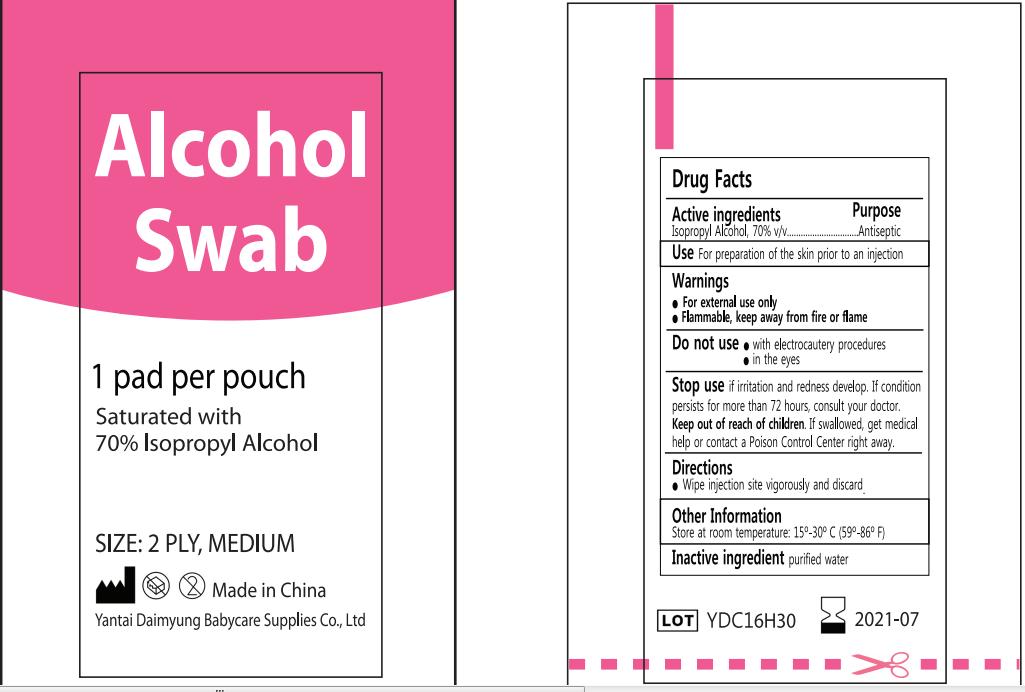 DRUG LABEL: Alcohol Swab
NDC: 70718-001 | Form: SWAB
Manufacturer: YANTAI DAIMYUNG BABYCARE SUPPLIES CO.,LTD.
Category: otc | Type: HUMAN OTC DRUG LABEL
Date: 20160818

ACTIVE INGREDIENTS: ISOPROPYL ALCOHOL 0.7 mL/1 1
INACTIVE INGREDIENTS: WATER

Active Ingredient

Isopropyl Alcohol 70%v/v

Purpose

Antiseptic

Use

For preparation of skin prior to injection.

WARNINGS

For External use only.

Flammable,keep away from fire or flame.

Do not use with electrocautery procedures in eyes.

Stop use and ask a doctor if irritation and redness develop,condition persists for more than 72 hours .

keep out of reach of children

In case of accidental ingestion, seek professional assistance or consult a PoisonControl Center immediately.

Directions

Wipe injection site vigorously and discard.

Inactive ingredients

purified water